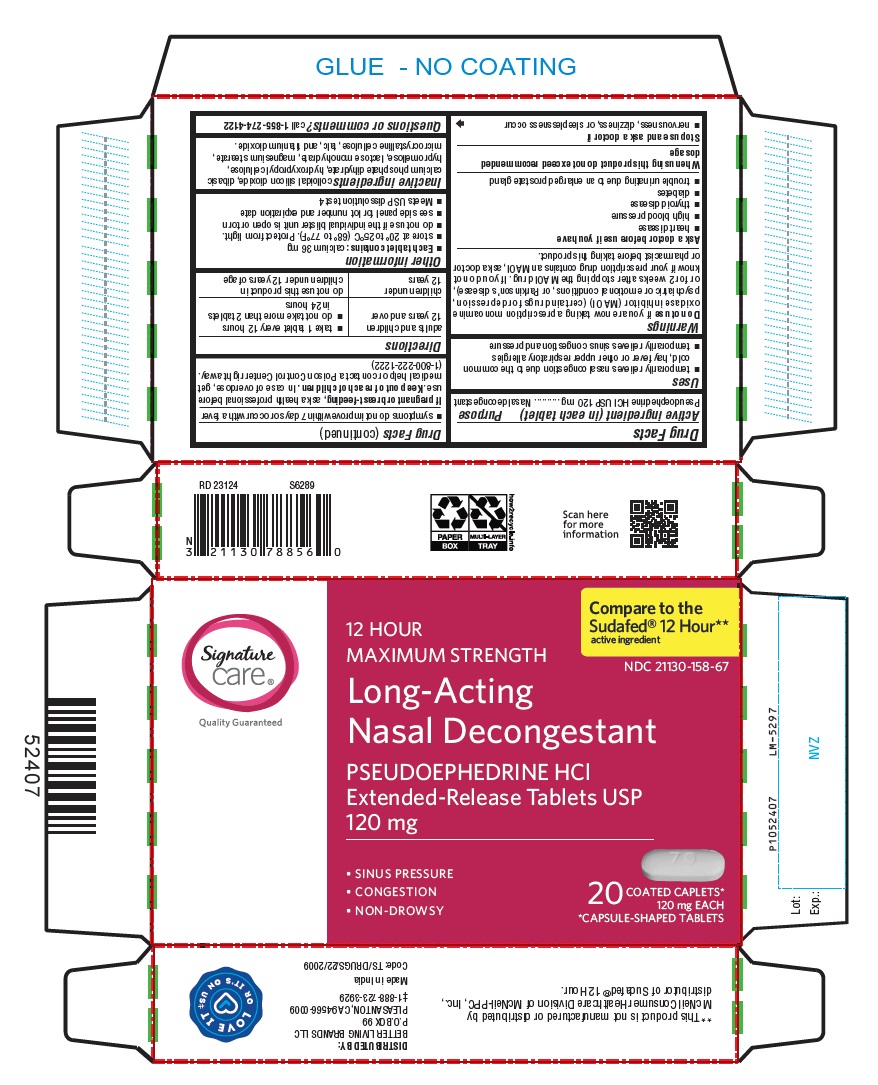 DRUG LABEL: Pseudoephedrine HCl
NDC: 21130-158 | Form: TABLET, EXTENDED RELEASE
Manufacturer: Better Living Brands LLC
Category: otc | Type: Human OTC Drug Label
Date: 20240724

ACTIVE INGREDIENTS: PSEUDOEPHEDRINE HYDROCHLORIDE 120 mg/1 1
INACTIVE INGREDIENTS: SILICON DIOXIDE; DIBASIC CALCIUM PHOSPHATE DIHYDRATE; HYDROXYPROPYL CELLULOSE (90000 WAMW); HYPROMELLOSE 2208 (15000 MPA.S); HYPROMELLOSE 2208 (4000 MPA.S); HYPROMELLOSE 2910 (5 MPA.S); LACTOSE MONOHYDRATE; MAGNESIUM STEARATE; MICROCRYSTALLINE CELLULOSE; TALC; TITANIUM DIOXIDE

Pseudoephedrine HCl Extended-Release Tablets USP 120 mg

Active ingredient (in each tablet)

Pseudoephedrine HCl USP 120 mg

Purpose

Nasal decongestant

Uses

- temporarily relieves nasal congestion due to the common cold, hay fever or other upper respiratory allergies
- temporarily relieves sinus congestion and pressure

Do not use

if you are now taking a prescription monoamine oxidase inhibitor (MAOI) (certain drugs for depression, psychiatric or emotional conditions, or Parkinson’s disease), or for 2 weeks after stopping the MAOI drug. If you do not know if your prescription drug contains an MAOI, ask a doctor or pharmacist before taking this product.

Ask a doctor before use if you have

- heart disease
- high blood pressure
- thyroid disease
- diabetes
- trouble urinating due to an enlarged prostate gland

Stop use and ask a doctor if

- nervousness, dizziness, or sleeplessness occur
- symptoms do not improve within 7 days or occur with a fever

If pregnant or breast-feeding,

ask a health professional before use.

Keep out of reach of children.

In case of overdose, get medical help or contact a Poison Control Center right away. (1-800-222-1222)

Directions

adults and children 12 years and over | - take 1 tablet every 12 hours - do not take more than 2 tablets in 24 hours
children under 12 years | do not use this product in children under 12 years of age

Other information

- Each tablet contains: calcium 36 mg
- store at 20° to 25°C (68° to 77°F). Protect from light.
- do not use if the individual blister unit is open or torn
- see side panel for lot number and expiration date
- Meets USP dissolution test 4

Inactive ingredients

colloidal silicon dioxide, dibasic calcium phosphate dihydrate, hydroxypropyl cellulose, hypromellose, lactose monohydrate, magnesium stearate, microcrystalline cellulose, talc, and titanium dioxide.

Questions or comments?

call 1-855-274-4122
DISTRIBUTED BY:
BETTER LIVING BRANDS LLC
P.O.BOX 99
PLEASANTON, CA 94566-0009
‡1-888-723-3929
Made in India
Code: TS/DRUGS/22/2009

PACKAGE LABEL-PRINCIPAL DISPLAY PANEL - 120 mg, Blister Carton 20 (2 X 10) Extended-Release Tablets

Compare to the
Sudafed® 12 Hour**
active ingredient
NDC 21130-158-67
12 HOUR
MAXIMUM STRENGTH
Long-Acting
Nasal Decongestant
PSEUDOEPHEDRINE HCl
Extended-Release Tablets USP
120 mg
• SINUS PRESSURE
• CONGESTION
• NON-DROWSY
20 COATED CAPLETS*
120 mg EACH
*CAPSULE-SHAPED TABLETS